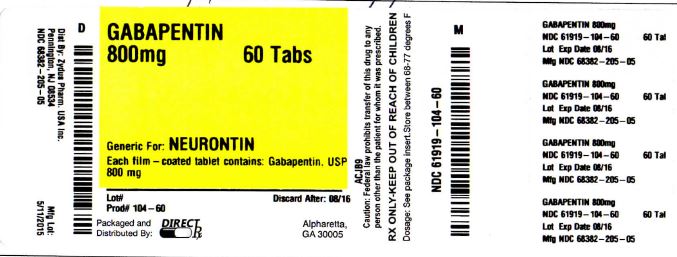 DRUG LABEL: GABAPENTIN
NDC: 61919-104 | Form: TABLET, FILM COATED
Manufacturer: DIRECT RX
Category: prescription | Type: HUMAN PRESCRIPTION DRUG LABEL
Date: 20151104

ACTIVE INGREDIENTS: GABAPENTIN 800 mg/1 1
INACTIVE INGREDIENTS: COPOVIDONE; HYDROXYPROPYL CELLULOSE, LOW SUBSTITUTED; MAGNESIUM STEARATE; MANNITOL; POLOXAMER 407; POVIDONE; TALC

GABAPENTIN

DESCRIPTION SECTION

Gabapentin is described as 1-(aminomethyl)cyclohexaneacetic acid with a molecular formula of C9H17NO2 and a molecular weight of 171.24. The structural formula of gabapentin is:

Gabapentin, USP is a white to off-white powder with a pKa1 of 3.7 and a pKa2 of 10.7. It is freely soluble in water, 0.1 N hydrochloric acid, 0.1 N sodium hydroxide and glacial acetic acid; slightly soluble in methanol, very slightly soluble in ethanol, 2-propanol; insoluble in toluene. The log of the partition coefficient (n-octanol/0.05M phosphate buffer) at pH 7.4 is –1.25.

Each gabapentin tablet, USP intended for oral administration contains 600 mg and 800 mg of gabapentin. In addition each tablet contains following inactive ingredients: copovidone, low substituted hydroxypropyl cellulose, magnesium stearate, mannitol, poloxamer, povidone and talc.

CLINICAL PHARMACOLOGY SECTION

Mechanism of Action

The mechanism by which gabapentin exerts its analgesic action is unknown, but in animal models of analgesia, gabapentin prevents allodynia (pain-related behavior in response to a normally innocuous stimulus) and hyperalgesia (exaggerated response to painful stimuli). In particular, gabapentin prevents pain-related responses in several models of neuropathic pain in rats or mice (e.g., spinal nerve ligation models, streptozocin-induced diabetes model, spinal cord injury model, acute herpes zoster infection model). Gabapentin also decreases pain-related responses after peripheral inflammation (carrageenan footpad test, late phase of formalin test). Gabapentin did not alter immediate pain-related behaviors (rat tail flick test, formalin footpad acute phase, acetic acid abdominal constriction test, footpad heat irradiation test). The relevance of these models to human pain is not known.

The mechanism by which gabapentin exerts its anticonvulsant action is unknown, but in animal test systems designed to detect anticonvulsant activity, gabapentin prevents seizures as do other marketed anticonvulsants. Gabapentin exhibits antiseizure activity in mice and rats in both the maximal electroshock and pentylenetetrazole seizure models and other preclinical models (e.g., strains with genetic epilepsy, etc.). The relevance of these models to human epilepsy is not known.

Gabapentin is structurally related to the neurotransmitter GABA (gamma-aminobutyric acid) but it does not modify GABAA or GABAB radioligand binding, it is not converted metabolically into GABA or a GABA agonist, and it is not an inhibitor of GABA uptake or degradation. Gabapentin was tested in radioligand binding assays at concentrations up to 100 µM and did not exhibit affinity for a number of other common receptor sites, including benzodiazepine, glutamate, N-methyl-D-aspartate (NMDA), quisqualate, kainate, strychnine-insensitive or strychnine-sensitive glycine, alpha 1, alpha 2, or beta adrenergic, adenosine A1 or A2, cholinergic muscarinic or nicotinic, dopamine D1 or D2, histamine H1, serotonin S1 or S2, opiate mu, delta or kappa, cannabinoid 1, voltage-sensitive calcium channel sites labeled with nitrendipine or diltiazem, or at voltage-sensitive sodium channel sites labeled with batrachotoxinin A 20-alpha-benzoate. Furthermore, gabapentin did not alter the cellular uptake of dopamine, noradrenaline, or serotonin.

In vitro studies with radiolabeled gabapentin have revealed a gabapentin binding site in areas of rat brain including neocortex and hippocampus. A high-affinity binding protein in animal brain tissue has been identified as an auxiliary subunit of voltage-activated calcium channels. However, functional correlates of gabapentin binding, if any, remain to be elucidated.

Pharmacokinetics and Drug Metabolism

All pharmacological actions following gabapentin administration are due to the activity of the parent compound; gabapentin is not appreciably metabolized in humans.

Oral Bioavailability

Gabapentin bioavailability is not dose proportional; i.e., as dose is increased, bioavailability decreases. Bioavailability of gabapentin is approximately 60%, 47%, 34%, 33%, and 27% following 900, 1200, 2400, 3600, and 4800 mg/day given in 3 divided doses, respectively. Food has only a slight effect on the rate and extent of absorption of gabapentin (14% increase in AUC and Cmax).

Distribution

Less than 3% of gabapentin circulates bound to plasma protein. The apparent volume of distribution of gabapentin after 150 mg intravenous administration is 58±6 L (Mean ±SD). In patients with epilepsy, steady-state predose (Cmin) concentrations of gabapentin in cerebrospinal fluid were approximately 20% of the corresponding plasma concentrations.

Elimination

Gabapentin is eliminated from the systemic circulation by renal excretion as unchanged drug. Gabapentin is not appreciably metabolized in humans.

Gabapentin elimination half-life is 5 to 7 hours and is unaltered by dose or following multiple dosing. Gabapentin elimination rate constant, plasma clearance, and renal clearance are directly proportional to creatinine clearance (see CLINICAL PHARMACOLOGY, Special Populations: Adult Patients With Renal Insufficiency, below). In elderly patients, and in patients with impaired renal function, gabapentin plasma clearance is reduced. Gabapentin can be removed from plasma by hemodialysis.

Dosage adjustment in patients with compromised renal function or undergoing hemodialysis is recommended (see DOSAGE AND ADMINISTRATION, Table 6).

Special PopulationsAdult Patients With Renal Insufficiency

Subjects (N=60) with renal insufficiency (mean creatinine clearance ranging from 13-114 mL/min) were administered single 400 mg oral doses of gabapentin. The mean gabapentin half- life ranged from about 6.5 hours (patients with creatinine clearance >60 mL/min) to 52 hours (creatinine clearance <30 mL/min) and gabapentin renal clearance from about 90 mL/min (>60 mL/min group) to about 10 mL/min (<30 mL/min). Mean plasma clearance (CL/F) decreased from approximately 190 mL/min to 20 mL/min.

Dosage adjustment in adult patients with compromised renal function is necessary (see DOSAGE AND ADMINISTRATION). Pediatric patients with renal insufficiency have not been studied.

Hemodialysis

In a study in anuric adult subjects (N=11), the apparent elimination half-life of gabapentin on nondialysis days was about 132 hours; during dialysis the apparent half-life of gabapentin was reduced to 3.8 hours. Hemodialysis thus has a significant effect on gabapentin elimination in anuric subjects.

Dosage adjustment in patients undergoing hemodialysis is necessary (see DOSAGE AND ADMINISTRATION).

Hepatic Disease

Because gabapentin is not metabolized, no study was performed in patients with hepatic impairment.

Age

The effect of age was studied in subjects 20-80 years of age. Apparent oral clearance (CL/F) of gabapentin decreased as age increased, from about 225 mL/min in those under 30 years of age to about 125 mL/min in those over 70 years of age. Renal clearance (CLr) and CLr adjusted for body surface area also declined with age; however, the decline in the renal clearance of gabapentin with age can largely be explained by the decline in renal function. Reduction of gabapentin dose may be required in patients who have age related compromised renal function. (see PRECAUTIONS, Geriatric Use and DOSAGE AND ADMINISTRATION).

Pediatric

Gabapentin pharmacokinetics were determined in 48 pediatric subjects between the ages of 1 month and 12 years following a dose of approximately 10 mg/kg. Peak plasma concentrations were similar across the entire age group and occurred 2 to 3 hours postdose. In general, pediatric subjects between 1 month and <5 years of age achieved approximately 30% lower exposure (AUC) than that observed in those 5 years of age and older. Accordingly, oral clearance normalized per body weight was higher in the younger children. Apparent oral clearance of gabapentin was directly proportional to creatinine clearance. Gabapentin elimination half-life averaged 4.7 hours and was similar across the age groups studied.

A population pharmacokinetic analysis was performed in 253 pediatric subjects between 1 month and 13 years of age. Patients received 10 to 65 mg/kg/day given TID. Apparent oral clearance (CL/F) was directly proportional to creatinine clearance and this relationship was similar following a single dose and at steady state. Higher oral clearance values were observed in children <5 years of age compared to those observed in children 5 years of age and older, when normalized per body weight. The clearance was highly variable in infants <1 year of age. The normalized CL/F values observed in pediatric patients 5 years of age and older were consistent with values observed in adults after a single dose. The oral volume of distribution normalized per body weight was constant across the age range.

These pharmacokinetic data indicate that the effective daily dose in pediatric patients with epilepsy ages 3 and 4 years should be 40 mg/kg/day to achieve average plasma concentrations similar to those achieved in patients 5 years of age and older receiving gabapentin at 30 mg/kg/day (see DOSAGE AND ADMINISTRATION).

Gender

Although no formal study has been conducted to compare the pharmacokinetics of gabapentin in men and women, it appears that the pharmacokinetic parameters for males and females are similar and there are no significant gender differences.

Race

Pharmacokinetic differences due to race have not been studied. Because gabapentin is primarily renally excreted and there are no important racial differences in creatinine clearance, pharmacokinetic differences due to race are not expected.

Clinical StudiesPostherpetic Neuralgia

Gabapentin tablets were evaluated for the management of postherpetic neuralgia (PHN) in 2 randomized, double-blind, placebo-controlled, multicenter studies; N=563 patients in the intent-to-treat (ITT) population (Table 1). Patients were enrolled if they continued to have pain for more than 3 months after healing of the herpes zoster skin rash.

Table 1 Controlled PHN Studies: Duration, Dosages, and Number of Patients
Study | Study Duration | Gabapentin (mg/day)a Target Dose | Patients Receiving Gabapentin | Patients Receiving Placebo
1 | 8 weeks | 3600 | 113 | 116
2 | 7 weeks | 1800, 2400 | 223 | 111
 |  | Total | 336 | 227
aGiven in 3 divided doses (TID)

Each study included a 1-week baseline during which patients were screened for eligibility and a 7- or 8-week double-blind phase (3 or 4 weeks of titration and 4 weeks of fixed dose). Patients initiated treatment with titration to a maximum of 900 mg/day gabapentin over 3 days. Dosages were then to be titrated in 600 to 1200 mg/day increments at 3- to 7-day intervals to target dose over 3 to 4 weeks. In Study 1, patients were continued on lower doses if not able to achieve the target dose. During baseline and treatment, patients recorded their pain in a daily diary using an 11-point numeric pain rating scale ranging from 0 (no pain) to 10 (worst possible pain). A mean pain score during baseline of at least 4 was required for randomization (baseline mean pain score for Studies 1 and 2 combined was 6.4). Analyses were conducted using the ITT population (all randomized patients who received at least one dose of study medication).

Both studies showed significant differences from placebo at all doses tested.

A significant reduction in weekly mean pain scores was seen by Week 1 in both studies, and significant differences were maintained to the end of treatment. Comparable treatment effects were observed in all active treatment arms. Pharmacokinetic/pharmacodynamic modeling provided confirmatory evidence of efficacy across all doses. Figures 1 and 2 show these changes for Studies 1 and 2.

Figure 1

Weekly Mean Pain Scores (Observed Cases in ITT Population): Study 1

Figure 2

Weekly Mean Pain Scores (Observed Cases in ITT Population): Study 2

The proportion of responders (those patients reporting at least 50% improvement in endpoint pain score compared with baseline) was calculated for each study (Figure 3).

Figure 3

Proportion of Responders (patients with ≥50% reduction in pain score) at Endpoint:

Controlled PHN Studies

Epilepsy

The effectiveness of gabapentin tablets as adjunctive therapy (added to other antiepileptic drugs) was established in multicenter placebo-controlled, double-blind, parallel-group clinical trials in adult and pediatric patients (3 years and older) with refractory partial seizures.

Evidence of effectiveness was obtained in three trials conducted in 705 patients (age 12 years and above) and one trial conducted in 247 pediatric patients (3 to 12 years of age). The patients enrolled had a history of at least 4 partial seizures per month in spite of receiving one or more antiepileptic drugs at therapeutic levels and were observed on their established antiepileptic drug regimen during a 12-week baseline period (6 weeks in the study of pediatric patients). In patients continuing to have at least 2 (or 4 in some studies) seizures per month, gabapentin tablet or placebo was then added on to the existing therapy during a 12-week treatment period. Effectiveness was assessed primarily on the basis of the percent of patients with a 50% or greater reduction in seizure frequency from baseline to treatment (the "responder rate") and a derived measure called response ratio, a measure of change defined as (T - B)/(T + B), in which B is the patient's baseline seizure frequency and T is the patient's seizure frequency during treatment. Response ratio is distributed within the range -1 to +1. A zero value indicates no change while complete elimination of seizures would give a value of -1; increased seizure rates would give positive values. A response ratio of -0.33 corresponds to a 50% reduction in seizure frequency. The results given below are for all partial seizures in the intent-to-treat (all patients who received any doses of treatment) population in each study, unless otherwise indicated.

One study compared gabapentin tablets 1200 mg/day divided TID with placebo. Responder rate was 23% (14/61) in the gabapentin tablets group and 9% (6/66) in the placebo group; the difference between groups was statistically significant. Response ratio was also better in the gabapentin tablets group (-0.199) than in the placebo group (-0.044), a difference that also achieved statistical significance.

A second study compared primarily 1200 mg/day divided TID gabapentin tablets (N=101) with placebo (N=98). Additional smaller gabapentin tablets dosage groups (600 mg/day, N=53; 1800 mg/day, N=54) were also studied for information regarding dose response. Responder rate was higher in the gabapentin tablets 1200 mg/day group (16%) than in the placebo group (8%), but the difference was not statistically significant. The responder rate at 600 mg (17%) was also not significantly higher than in the placebo, but the responder rate in the 1800 mg group (26%) was statistically significantly superior to the placebo rate. Response ratio was better in the gabapentin tablets 1200 mg/day group (-0.103) than in the placebo group (-0.022); but this difference was also not statistically significant (p = 0.224). A better response was seen in the gabapentin tablets 600 mg/day group (-0.105) and 1800 mg/day group (-0.222) than in the 1200 mg/day group, with the 1800 mg/day group achieving statistical significance compared to the placebo group.

A third study compared gabapentin tablets 900 mg/day divided TID (N=111) and placebo (N=109). An additional gabapentin tablets 1200 mg/day dosage group (N=52) provided dose-response data. A statistically significant difference in responder rate was seen in the gabapentin tablets 900 mg/day group (22%) compared to that in the placebo group (10%). Response ratio was also statistically significantly superior in the gabapentin tablets 900 mg/day group (-0.119) compared to that in the placebo group (-0.027), as was response ratio in 1200 mg/day gabapentin tablets (-0.184) compared to placebo.

Analyses were also performed in each study to examine the effect of gabapentin tablets on preventing secondarily generalized tonic-clonic seizures. Patients who experienced a secondarily generalized tonic-clonic seizure in either the baseline or in the treatment period in all three placebo-controlled studies were included in these analyses. There were several response ratio comparisons that showed a statistically significant advantage for gabapentin tablets compared to placebo and favorable trends for almost all comparisons.

Analysis of responder rate using combined data from all three studies and all doses (N=162, gabapentin tablets; N=89, placebo) also showed a significant advantage for gabapentin tablets over placebo in reducing the frequency of secondarily generalized tonic-clonic seizures.

In two of the three controlled studies, more than one dose of gabapentin tablets was used. Within each study, the results did not show a consistently increased response to dose. However, looking across studies, a trend toward increasing efficacy with increasing dose is evident (see Figure 4).

Figure 4

Responder Rate in Patients Receiving Gabapentin Tablets Expressed as a Difference from Placebo by Dose and Study: Adjunctive Therapy Studies in Patients ≥12 Years of Age with Partial Seizures

In the figure, treatment effect magnitude, measured on the Y axis in terms of the difference in the proportion of gabapentin and placebo-assigned patients attaining a 50% or greater reduction in seizure frequency from baseline, is plotted against the daily dose of gabapentin administered (X axis).

Although no formal analysis by gender has been performed, estimates of response (Response Ratio) derived from clinical trials (398 men, 307 women) indicate no important gender differences exist. There was no consistent pattern indicating that age had any effect on the response to gabapentin. There were insufficient numbers of patients of races other than Caucasian to permit a comparison of efficacy among racial groups.

A fourth study in pediatric patients age 3 to 12 years compared 25 - 35 mg/kg/day gabapentin tablets (N=118) with placebo (N=127). For all partial seizures in the intent-to-treat population, the response ratio was statistically significantly better for the gabapentin tablets group (-0.146) than for the placebo group (-0.079). For the same population, the responder rate for gabapentin tablets (21%) was not significantly different from placebo (18%).

A study in pediatric patients age 1 month to 3 years compared 40 mg/kg/day gabapentin tablets (N=38) with placebo (N=38) in patients who were receiving at least one marketed antiepileptic drug and had at least one partial seizure during the screening period (within 2 weeks prior to baseline). Patients had up to 48 hours of baseline and up to 72 hours of double-blind video EEG monitoring to record and count the occurrence of seizures. There were no statistically significant differences between treatments in either the response ratio or responder rate.

DRUG ABUSE AND DEPENDENCE SECTION

Controlled Substance

Gabapentin is not a scheduled drug.

Abuse

Gabapentin does not exhibit affinity for benzodiazepine, opiate (mu, delta or kappa), or cannabinoid 1 receptor sites. A small number of postmarketing cases report gabapentin misuse and abuse. These individuals were taking higher than recommended doses of gabapentin for unapproved uses. Most of the individuals described in these reports had a history of poly-substance abuse or used gabapentin to relieve symptoms of withdrawal from other substances. When prescribing gabapentin carefully evaluate patients for a history of drug abuse and observe them for signs and symptoms of gabapentin misuse or abuse (e.g. development of tolerance, self-dose escalation, and drug-seeking behavior).

Dependence

There are rare postmarketing reports of individuals experiencing withdrawal symptoms shortly after discontinuing higher than recommended doses of gabapentin used to treat illnesses for which the drug is not approved. Such symptoms included agitation, disorientation and confusion after suddenly discontinuing gabapentin that resolved after restarting gabapentin. Most of these individuals had a history of poly-substance abuse or used gabapentin to relieve symptoms of withdrawal from other substances. The dependence and abuse potential of gabapentin has not been evaluated in human studies.

OVERDOSAGE SECTION

A lethal dose of gabapentin was not identified in mice and rats receiving single oral doses as high as 8000 mg/kg. Signs of acute toxicity in animals included ataxia, labored breathing, ptosis, sedation, hypoactivity, or excitation.

Acute oral overdoses of gabapentin tablets up to 49 grams have been reported. In these cases, double vision, slurred speech, drowsiness, lethargy and diarrhea, were observed. All patients recovered with supportive care.

Gabapentin can be removed by hemodialysis. Although hemodialysis has not been performed in the few overdose cases reported, it may be indicated by the patient's clinical state or in patients with significant renal impairment.

DOSAGE & ADMINISTRATION SECTION

Gabapentin tablets are given orally with or without food. Patients should be informed that, should they break the scored 600 or 800 mg tablet in order to administer a half-tablet, they should take the unused half-tablet as the next dose. Half-tablets not used within several days of breaking the scored tablet should be discarded.

If gabapentin tablets dose is reduced, discontinued, or substituted with an alternative medication, this should be done gradually over a minimum of 1 week (a longer period may be needed at the discretion of the prescriber).

Postherpetic Neuralgia

In adults with postherpetic neuralgia, gabapentin therapy may be initiated as a single 300-mg dose on Day 1, 600 mg/day on Day 2 (divided BID), and 900 mg/day on Day 3 (divided TID). The dose can subsequently be titrated up as needed for pain relief to a daily dose of 1800 mg (divided TID). In clinical studies, efficacy was demonstrated over a range of doses from 1800 mg/day to 3600 mg/day with comparable effects across the dose range. Additional benefit of using doses greater than 1800 mg/day was not demonstrated.

Epilepsy

Gabapentin tablets are recommended for add-on therapy in patients 3 years of age and older. Effectiveness in pediatric patients below the age of 3 years has not been established.

Patients >12 years of age

The effective dose of gabapentin is 900 to 1800 mg/day and given in divided doses (three times a day) using 300 or 400 mg capsules, or 600 or 800 mg tablets. The starting dose is 300 mg three times a day. If necessary, the dose may be increased using 300 or 400 mg capsules, or 600 or 800 mg tablets three times a day up to 1800 mg/day. Dosages up to 2400 mg/day have been well tolerated in long-term clinical studies. Doses of 3600 mg/day have also been administered to a small number of patients for a relatively short duration, and have been well tolerated. The maximum time between doses in the TID schedule should not exceed 12 hours.

Pediatric Patients Age 3 to 12 years

The starting dose should range from 10-15 mg/kg/day in 3 divided doses, and the effective dose reached by upward titration over a period of approximately 3 days. The effective dose of gabapentin tablets in patients 5 years of age and older is 25–35 mg/kg/day and given in divided doses (three times a day). The effective dose in pediatric patients ages 3 and 4 years is 40 mg/kg/day and given in divided doses (three times a day) (see CLINICAL PHARMACOLOGY, Pediatrics). Dosages up to 50 mg/kg/day have been well tolerated in a long-term clinical study. The maximum time interval between doses should not exceed 12 hours.

It is not necessary to monitor gabapentin plasma concentrations to optimize gabapentin therapy. Further, because there are no significant pharmacokinetic interactions among gabapentin and other commonly used antiepileptic drugs, the addition of gabapentin does not alter the plasma levels of these drugs appreciably.

If gabapentin tablets are discontinued and/or an alternate anticonvulsant medication is added to the therapy, this should be done gradually over a minimum of 1 week.

Dosage in Renal Impairment

Creatinine clearance is difficult to measure in outpatients. In patients with stable renal function, creatinine clearance (CCr) can be reasonably well estimated using the equation of Cockcroft and Gault:

for females CCr=(0.85)(140-age)(weight)/[(72)(SCr)]

for males CCr=(140-age)(weight)/[(72)(SCr)]

in which age is in years, weight is in kilograms and SCr is serum creatinine in mg/dL.

Dosage adjustment in patients ≥12 years of age with compromised renal function or undergoing hemodialysis is recommended as follows (see dosing recommendations above for effective doses in each indication).

Table 6 Gabapentin Tablets Dosage Based on Renal Function
Renal Function Creatinine Clearance (mL/min) | Total Daily Dose Range (mg/day) | Dose Regimen (mg)
≥60 | 900-3600 | 300 TID | 400 TID | 600 TID | 800 TID | 1200 TID
>30-59 | 400-1400 | 200 BID | 300 BID | 400 BID | 500 BID | 700 BID
>15-29 | 200-700 | 200 QD | 300 QD | 400 QD | 500 QD | 700 QD
15a | 100-300 | 100 QD | 125 QD | 150 QD | 200 QD | 300 QD
 |  |  |  | Post-Hemodialysis Supplemental Dose (mg)b
Hemodialysis |  | 125b | 150b | 200b | 250b | 350b
a For patients with creatinine clearance <15 mL/min, reduce daily dose in proportion to creatinine clearance (e.g., patients with a creatinine clearance of 7.5 mL/min should receive one-half the daily dose that patients with a creatinine clearance of 15 mL/min receive).
b Patients on hemodialysis should receive maintenance doses based on estimates of creatinine clearance as indicated in the upper portion of the table and a supplemental post-hemodialysis dose administered after each 4 hours of hemodialysis as indicated in the lower portion of the table.

The use of gabapentin tablets in patients <12 years of age with compromised renal function has not been studied.

Dosage in Elderly

Because elderly patients are more likely to have decreased renal function, care should be taken in dose selection, and dose should be adjusted based on creatinine clearance values in these patients.

HOW SUPPLIED SECTION

Gabapentin Tablets, USP 600 mg are white to off-white having mottled spots, oval-shaped, biconvex, film-coated tablets debossed with 'ZE72' with bisect on one side and plain with bisect on other side and are supplied as follows:

NDC 68382-204-01 in bottle of 100 tablets

NDC 68382-204-05 in bottle of 500 tablets

NDC 68382-204-10 in bottle of 1000 tablets

Gabapentin Tablets, USP 800 mg are white to off-white having mottled spots, oval-shaped, bevelled-edge, biconvex, film-coated tablets debossed with 'ZE71' with bisect on one side and plain with bisect on other side and are supplied as follows:

NDC 68382-205-01 in bottle of 100 tablets

NDC 68382-205-05 in bottle of 500 tablets

NDC 68382-205-10 in bottle of 1000 tablets

NDC 68382-205-30 in unit-dose blister cartons of 100 (10 x 10) unit dose tablets

STORAGE AND HANDLING SECTION

Store at 20° to 25°C (68° to 77°F) [See USP Controlled Room Temperature].

Dispense in a tight container.

Call your doctor for medical advice about side effects. You may report side effects to FDA at 1-800-FDA-1088.

Manufactured by:

Cadila Healthcare Ltd.

Ahmedabad, India

Distributed by:

Zydus Pharmaceuticals USA Inc.

Pennington, NJ 08534

Rev.: 04/14

Revision Date: 2014/04/05

SPL MEDGUIDE SECTION

Gabapentin Tablets, USP

Read the Medication Guide before you start taking gabapentin tablets and each time you get a refill. There may be new information. This information does not take the place of talking to your healthcare provider about your medical condition or treatment.

What is the most important information I should know about Gabapentin Tablets? Do not stop taking gabapentin tablets without first talking to your healthcare provider.

Stopping gabapentin tablets suddenly can cause serious problems.

Gabapentin tablets can cause serious side effects including:

1. Like other antiepileptic drugs, gabapentin tablets may cause suicidal thoughts or actions in a very small number of people, about 1 in 500.

Call a healthcare provider right away if you have any of these symptoms, especially if they are new, worse, or worry you:

- thoughts about suicide or dying
- attempts to commit suicide
- new or worse depression
- new or worse anxiety
- feeling agitated or restless
- panic attacks
- trouble sleeping (insomnia)
- new or worse irritability
- acting aggressive, being angry, or violent
- acting on dangerous impulses
- an extreme increase in activity and talking (mania)
- other unusual changes in behavior or mood

How can I watch for early symptoms of suicidal thoughts and actions?

- Pay attention to any changes, especially sudden changes, in mood, behaviors, thoughts, or feelings.
- Keep all follow-up visits with your healthcare provider as scheduled.

Call your healthcare provider between visits as needed, especially if you are worried about symptoms.

Do not stop taking gabapentin tablets without first talking to a healthcare provider.

- Stopping gabapentin tablets suddenly can cause serious problems. Stopping a seizure medicine suddenly in a patient who has epilepsy can cause seizures that will not stop (status epilepticus).

Suicidal thoughts or actions can be caused by things other than medicines. If you have suicidal thoughts or actions, your healthcare provider may check for other causes.

2. Changes in behavior and thinking -Using gabapentin tablets in children 3 to 12 years of age can cause emotional changes, aggressive behavior, problems with concentration, restlessness, changes in school performance, and hyperactivity.

3. Gabapentin may cause a serious or life-threatening allergic reaction that may affect your skin or other parts of your body such as your liver or blood cells. You may or may not have rash when you get this type of reaction. It may cause you to be hospitalized or to stop gabapentin. Call a healthcare provider right away if you have any of the following symptoms:

- skin rash
- hives
- fever
- swollen glands that do not go away
- swelling of your lip and tongue
- yellowing of your skin or of the whites of the eyes
- unusual bruising or bleeding
- severe fatigue or weakness
- unexpected muscle pain
- frequent infections

These symptoms may be the first signs of a serious reaction. A healthcare provider should examine you to decide if you should continue taking gabapentin.

What is Gabapentin Tablets?

Gabapentin tablets is a prescription medicine used to treat:

- Pain from damaged nerves (postherpetic pain) that follows healing of shingles (a painful rash that comes after a herpes zoster infection) in adults.
- Partial seizures when taken together with other medicines in adults and children 3 years of age and older.

Who should not take Gabapentin Tablets?

Do not take gabapentin tablets if you are allergic to gabapentin or any of the other ingredients in gabapentin tablets. See the end of this Medication Guide for a complete list of ingredients in gabapentin tablets.

What should I tell my healthcare provider before taking Gabapentin Tablets?

Before taking gabapentin tablets, tell your healthcare provider if you:

- have or have had kidney problems or are on hemodialysis
- have or have had depression, mood problems, or suicidal thoughts or behavior
- are pregnant or plan to become pregnant. It is not known if gabapentin tablets can harm your unborn baby. Tell your healthcare provider right away if you become pregnant while taking gabapentin tablets. You and your healthcare provider will decide if you should take gabapentin tablets while you are pregnant.
- If you become pregnant while taking gabapentin tablets, talk to your healthcare provider about registering with the North American Antiepileptic Drug (NAAED) Pregnancy Registry. The purpose of this registry is to collect information about the safety of antiepileptic drugs during pregnancy. You can enroll in this registry by calling 1-888-233-2334.
- are breastfeeding or plan to breastfeed. Gabapentin tablets can pass into breast milk. You and your healthcare provider should decide how you will feed your baby while you take gabapentin tablets.

Tell your healthcare provider about all the medicines you take, including prescription and non-prescription medicines, vitamins, and herbal supplements.

Taking gabapentin tablets with certain other medicines can cause side effects or affect how well they work. Do not start or stop other medicines without talking to your healthcare provider.

Know the medicines you take. Keep a list of them and show it to your healthcare provider and pharmacist when you get a new medicine.

How should I take Gabapentin Tablets?

- Take gabapentin tablets exactly as prescribed. Your healthcare provider will tell you how much gabapentin tablets to take.
- Do not change your dose of gabapentin tablets without talking to your healthcare provider. If you break a tablet in half, the unused half of the tablet should be taken at your next scheduled dose. Half tablets not used within several days of breaking should be thrown away.
- Gabapentin tablets can be taken with or without food. If you take an antacid containing aluminum and magnesium, such as Maalox®*, Mylanta®*, Gelusil®*, Gaviscon®*, or Di-Gel®*, you should wait at least 2 hours before taking your next dose of gabapentin tablets.
- If you take too much gabapentin tablets, call your healthcare provider or your local Poison Control Center right away.

What should I avoid while taking Gabapentin Tablets?

- Do not drink alcohol or take other medicines that make you sleepy or dizzy while taking gabapentin tablets without first talking with your healthcare provider. Taking gabapentin tablets with alcohol or drugs that cause sleepiness or dizziness may make your sleepiness or dizziness worse.
- Do not drive, operate heavy machinery, or do other dangerous activities until you know how gabapentin tablet affects you. Gabapentin tablets can slow your thinking and motor skills.

What are the possible side effects of Gabapentin Tablets?

- See "What is the most important information I should know about Gabapentin Tablets?"
- The most common side effects of gabapentin tablets include:
- dizziness
- difficulty with speaking
- lack of coordination
- temporary loss of memory (amnesia)
- viral infection
- tremor
- feeling drowsy
- difficulty with coordination
- feeling tired
- double vision
- fever
- unusual eye movement
- jerky movements

Tell your healthcare provider if you have any side effect that bothers you or that does not go away.

These are not all the possible side effects of gabapentin tablets. For more information, ask your healthcare provider or pharmacist.

Call your doctor for medical advice about side effects. You may report side effects to FDA at 1-800-FDA-1088.

How should I store Gabapentin Tablets?

Store gabapentin tablets at 20° to 25°C (68° to 77°F) [See USP Controlled Room Temperature].

Dispense in a tight container.

Keep Gabapentin Tablets and all medicines out of the reach of children.

General information about the safe and effective use of Gabapentin Tablets

Medicines are sometimes prescribed for purposes other than those listed in a Medication Guide. Do not use gabapentin tablets for a condition for which it was not prescribed. Do not give gabapentin tablets to other people, even if they have the same symptoms that you have. It may harm them.

This Medication Guide summarizes the most important information about gabapentin tablets. If you would like more information, talk with your healthcare provider. You can ask your healthcare provider or pharmacist for information about gabapentin tablets that was written for healthcare professionals. Please address medical inquiries to, (MedicalAffairs@zydususa.com) Tel.:1-877-993-8779.

What are the ingredients in Gabapentin Tablets?

Active ingredient: gabapentin, USP

Inactive ingredients: copovidone, low substituted hydroxypropyl cellulose, magnesium stearate, mannitol, poloxamer, povidone and talc

*All trademarks are the property of their respective owners.

This Medication Guide has been approved by the U.S. Food and Drug Administration.

This product's label may have been updated. For current full prescribing information, please visit www.zydususa.com.

Manufactured by:

Cadila Healthcare Ltd.

Ahmedabad, India

Distributed by:

Zydus Pharmaceuticals USA Inc.

Pennington, NJ 08534

Rev.: 07/13

Revision Date: 2013/07/05

PACKAGE LABEL.PRINCIPAL DISPLAY PANEL

NDC 68382-204-01 in bottle of 100 tablets

Gabapentin Tablets USP, 600 mg

Rx only

100 tablets

ZYDUS